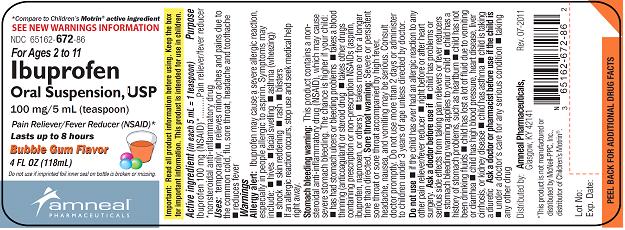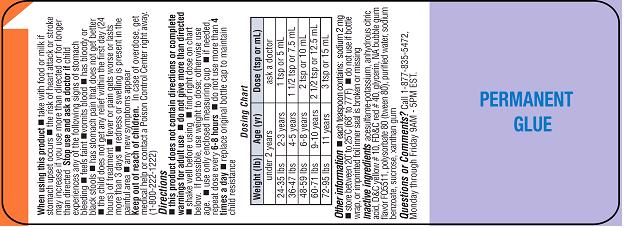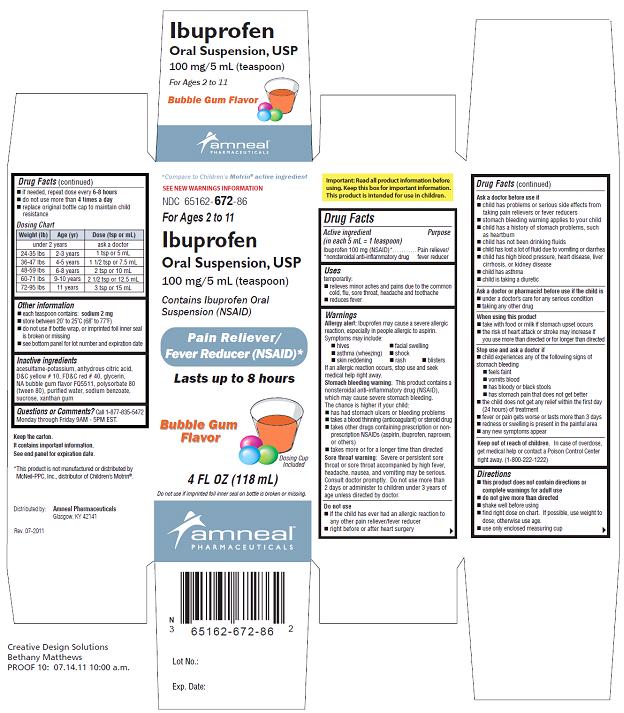 DRUG LABEL: Ibuprofen
NDC: 65162-672 | Form: SUSPENSION
Manufacturer: Amneal Pharmaceuticals
Category: otc | Type: HUMAN OTC DRUG LABEL
Date: 20120221

ACTIVE INGREDIENTS: IBUPROFEN 100 mg/5 mL
INACTIVE INGREDIENTS: ACESULFAME POTASSIUM; ANHYDROUS CITRIC ACID; D&C YELLOW NO. 10; FD&C RED NO. 40; GLYCERIN; POLYSORBATE 80; WATER; SODIUM BENZOATE; SUCROSE; XANTHAN GUM

Ibuprofen Oral Suspension, USP (NSAID)
Pain Reliever/ Fever Reducer
100 mg/ 5 mL

OTC - ACTIVE INGREDIENT

Active Ingredient

(in each 5 mL = 1 teaspoon)

Ibuprofen 100 mg (NSAID)*

*nonsteroidal anti-inflammatory drug

OTC - PURPOSE

Purpose

Pain reliever/ fever reducer

INDICATIONS AND USAGE

Uses

Temporarily:

■ Relieves minor aches and pains due to the common cold, flu, sore throat, headache and toothache

■ Reduces fever

WARNINGS

Warnings

Allergy alert:

Ibuprofen may cause a severe allergic reaction, especially in people allergic to aspirin.

Symptoms may include:

■ hives ■ facial swelling

■ asthma (wheezing) ■ shock

■ skin reddening ■ rash ■ blisters

If an allergic reaction occurs, stop use and seek medical help right away.

Stomach bleeding warning:

This product contains a nonsteroidal anti-inflammatory drug (NSAID), which may cause severe stomach bleeding. The chances are higher if your child:

■ has had stomach ulcers or bleeding problems

■ takes a blood thinning (anticoagulant) or steroid drug

■ takes other drugs containing an NSAID (aspirin, ibuprofen, naproxen, or others)

■ takes more or for a longer time than directed

Sore throat warning:

Severe or persistent sore throat or sore throat accompanied by high fever, headache, nausea, and vomiting may be serious. Consult doctor promptly. Do not use more than 2 days or administer to children under 3 years of age unless directed by doctor.

OTC - DO NOT USE

Do not use:

■ if the child has ever had an allergic reaction to any other pain reliever/fever reducer

■ right before or after heart surgery

OTC - ASK DOCTOR

Ask a doctor before use if:

■ child has problems or serious side effects from taking pain relievers or fever reducers

■ stomach bleeding warning applies to your child

■ child has a history of stomach problems, such as heartburn

■ child has not been drinking fluids

■ child has lost a lot of fluid due to vomiting or diarrhea

■ child has high blood pressure, heart disease, liver cirrhosis, or kidney disease

■ child has asthma

■ child is taking a diuretic

OTC - ASK DOCTOR/PHARMACIST

Ask a doctor or pharmacist before use if the child is:

■ under doctor’s care for any serious condition

■ taking any other drug

OTC - WHEN USING

When using this product:

■ take with food or milk if stomach upset occurs

■ the risk of heart attack or stroke may increase if you use more than directed or for longer than directed

OTC - STOP USE

Stop use and ask a doctor if:

■ child experiences any of the following signs of stomach bleeding

■ feels faint ■ vomits blood ■ has bloody or black stools

■ has stomach pain that does not get better

■ the child does not get any relief within the first day (24 hours) of treatment

■ fever or pain gets worse or lasts more than 3 days

■ redness or swelling is present in the painful area

■ any new symptoms appear

OTC - KEEP OUT OF REACH OF CHILDREN

Keep out of reach of children. In case of overdose, get medical help or contact a Poison Control Center right away. (1-800-222-1222)

DOSAGE AND ADMINISTRATION

Directions

■ this product does not contain directions or complete warnings for adult use

■ do not give more than directed

■ shake well before using

■ find right dose on chart below (if possible, use weight to dose; otherwise use age)

■ use only enclosed measuring cup

■ if needed, repeat dose every 6-8 hours

■ do not use more than 4 times a day

■ replace original bottle cap to maintain child resistance

Dosing Chart

Weight (lb) | Age (yr) | Dose (tsp or mL)
under 2 years |  | ask a doctor
24-35 lbs | 2-3 years | 1 tsp or 5 mL
36-47 lbs | 4-5 years | 1 ½ tsp or 7.5 mL
48-59 lbs | 6-8 years | 2 tsp or 10 mL
60-71 lbs | 9-10 years | 2 ½ tsp or 12.5 mL
72-95 lbs | 11 years | 3 tsp or 15 mL

OTHER INFORMATION

Other information

■ each teaspoon contains: sodium 2 mg

■ store between 20° to 25°C (68° to 77°F)

■ do not use if bottle wrap, or imprinted foil inner seal is broken or missing

■ see bottom panel for lot number and expiration date

INACTIVE INGREDIENTS

acesulfame-potassium, anhydrous citric acid, D&C yellow # 10, FD&C red # 40, glycerin, NA bubble gum flavor FQ5511, polysorbate 80 (tween 80), purified water, sodium benzoate, sucrose, xanthan gum

OTC - QUESTIONS

Questions or Comments? Call 1-877-835-5472,

Monday through Friday 9AM - 5PM EST.

Keep the carton.

It contains important information.

See end panel for expiration date.

*This product is not manufactured or distributed by McNeil-PPC, Inc., distributor of Children’s Motrin®.

Distributed by: Amneal Pharmaceuticals

Glasgow, KY 42141

Rev. 07-2011